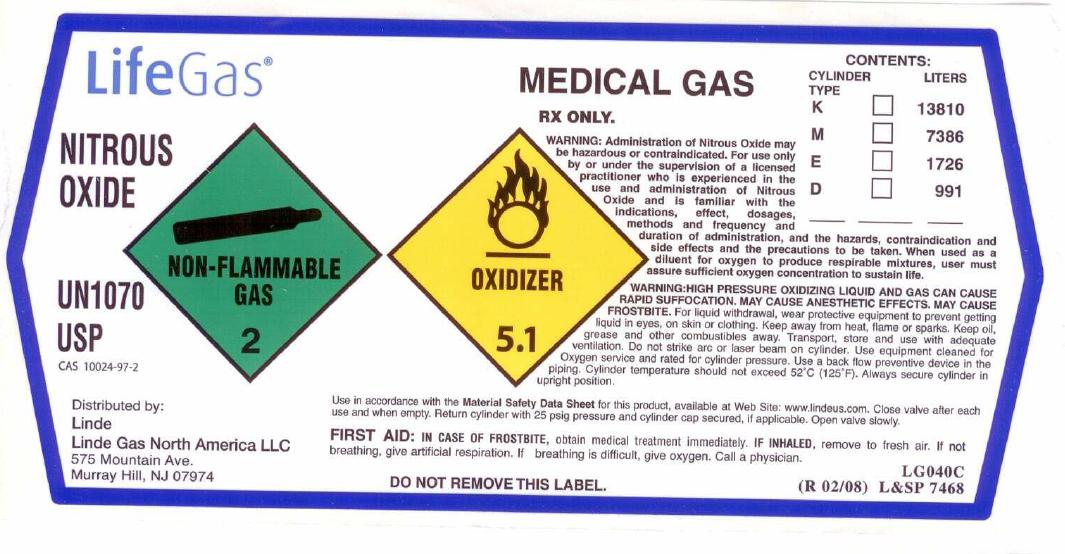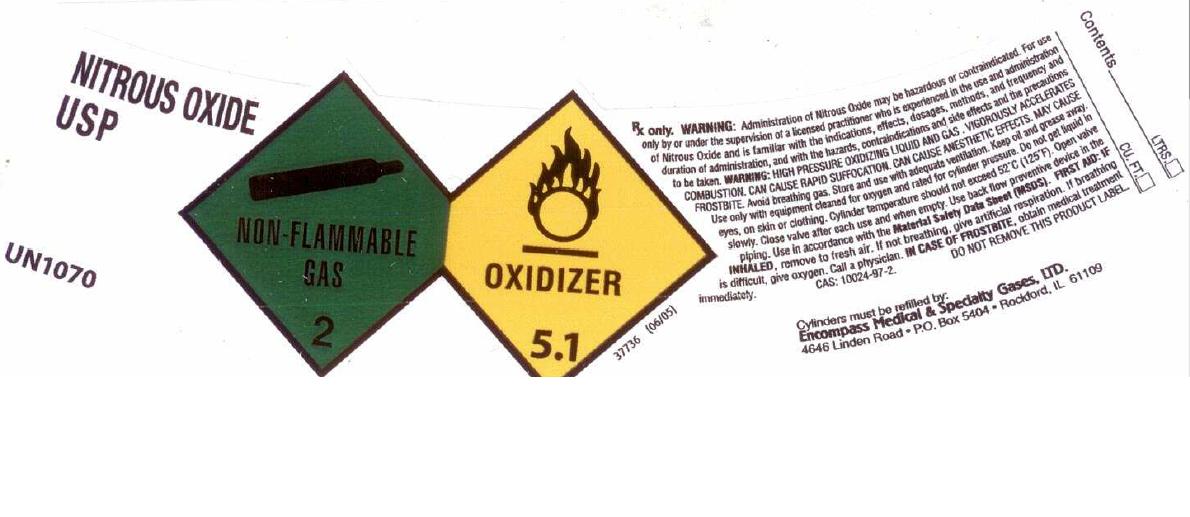 DRUG LABEL: Nitrous Oxide
NDC: 48883-004 | Form: GAS
Manufacturer: Encompass Medical & Specialty Gases, Ltd.
Category: prescription | Type: HUMAN PRESCRIPTION DRUG LABEL
Date: 20101203

ACTIVE INGREDIENTS: Nitrous Oxide 990 mL/1 L

Nitrous Oxide Label

PACKAGE LABEL

LifeGas
NITROUS OXIDE UN1070
USP CAS: 10024-97-2
Distributed by: Linde Linde Gas North America LLC 575 Mountain Ave. Murray Hill, NJ 07974
NON-FLAMMABLE GAS 2 OXIDIZER 5.1
MEDICAL GAS
Rx only. WARNING: Administration of Nitrous Oxide may be hazardous or contraindicated. For use only by or under the supervision of a licensed practitioner who is experienced in the use and administration of Nitrous Oxide and is familiar with the indications, effects, dosages, methods, and frequency and duration of administration, and with the hazards, contraindications and side effects and the precautions to be taken. When used as a diluent for oxygen to produce respirable mixtures, user must assure sufficient oxygen concentration to sustain life.
WARNING: HIGH PRESSURE OXIDIZING LIQUID AND GAS. CAN CAUSE RAPID SUFFOCATION. MAY CAUSE ANESTHETIC EFFECTS. MAY CAUSE FROSTBITE. For liquid withdrawal, wear protective equipment to prevent getting liquid in eyes, on skin or clothing. Keep away from heat, flame or sparks. Keep oil, grease and other combustibles away. Transport, store and use with adequate ventilation. Do not strike arc or laser beam on cylinder. Use equipment cleaned for Oxygen service and rated for cylinder pressure. . Use a back flow preventive device in the piping. Cylinder temperature should not exceed 52C (125F). Always secure cylinder in upright position. Use in accordance with the Material Safety Data Sheets for this product, available at Web Site: www.lindeus.com. Close valve after each use and when empty. Return cylinder with 25 psig pressure and cylinder cap secured, if applicable. Open valve slowly.
FIRST AID: IN CASE OF FROSTBITE, obtain medical treatment immediately.
IF INHALED, remove to fresh air. If not breathing, give artificial respiration. If breathing is difficult, give oxygen. Call a physician.
DO NOT REMOVE THIS LABEL.
LG040C (R 02/08) L and SP 7468

PACKAGE LABEL

NITROUS OXIDE USP UN1070
NON-FLAMMABLE GAS 2 OXIDIZER 5.1 37736 (06/05)
Rx only. WARNING: Administration of Nitrous Oxide may be hazardous or contraindicated. For use only by or under the supervision of a licensed practitioner who is experienced in the use and administration of Nitrous Oxide and is familiar with the indications, effects, dosages, methods, and frequency and duration of administration, and with the hazards, contraindications and side effects and the precautions to be taken.
WARNING: HIGH PRESSURE OXIDIZING LIQUID AND GAS. VIGOROUSLY ACCELERATES COMBUSTION. CAN CAUSE RAPID SUFFOCATION. CAN CAUSE ANESTHETIC EFFECTS. MAY CAUSE FROSTBITE. Avoid breathing gas. Store and use with adequate ventilation. Keep oil and grease away. Use only with equipment cleaned for oxygen and rated for cylinder pressure. Do not get liquid in eyes, on skin, or clothing. Cylinder temperature should not exceed 52C (125F). Open valve slowly. Close valve after each use and when empty. Use a back flow preventive device in the piping. Use in accordance with the Material Safety Data Sheets (MSDS).
FIRST AID: IF INHALED, remove to fresh air. If not breathing, give artificial respiration. If breathing is difficult, give oxygen. Call a physician. IN CASE OF FROSTBITE, obtain medical treatment immediately.
CAS: 10024-97-2
DO NOT REMOVE THIS PRODUCT LABEL.
Cylinders must be refilled by:
Encompass Medical and Specialty Gases, LTD. 4646 Linden Road P.O. Box 5404 Rockford, IL 61109
CONTENTS: LTRS. CU. FT.